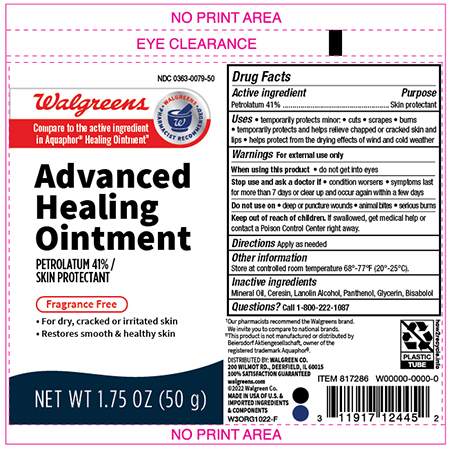 DRUG LABEL: Walgreens Baby Healing
NDC: 0363-0079 | Form: OINTMENT
Manufacturer: Walgreens Company
Category: otc | Type: HUMAN OTC DRUG LABEL
Date: 20241120

ACTIVE INGREDIENTS: PETROLATUM 410 mg/1 g
INACTIVE INGREDIENTS: LIGHT MINERAL OIL; CERESIN; LANOLIN ALCOHOLS; GLYCERIN; PANTHENOL; LEVOMENOL

Active Ingredient

Petrolatum - 41%

Purpose

Skin Protectant

Uses

• temporarily protects minor:

• cuts • scrapes • burns

• temporarily protects and helps relieve chapped or cracked skin and lips

• helps protect from the drying effects of wind and cold weather

• helps treat and prevent diaper rash

• protects chafed skin associated with diaper rash and helps protect from wetness

Directions

- apply as needed for diaper rash, use change wet or soiled diapers promptly cleanse the diaper area, and allow to dry.Apply ointment liberally as often as nessary, with each diaper change, especially at bedtime or anytime when exposed to wet diapers may be prolonged

Warnings

For External Use Only

When using this product

- Do not get into eyes

Stop Use and ask a Doctor if

- conditions worsens
- symptoms last more than 7 days or clear up an occur again within a few days

Do not use on

deep punture wounds
animal bites
serious burns

Keep out of the reach of children

If swallowed, get medical help
or contact a Poison Control Center right away.

Inactive Ingredients

Mineral Oil, Ceresin, Lanolin Alcohol, Panthenol, Glycerin, Bisabolol

Other information

Store at controlled room temperature 68°-77°F(20-25C)

Principal Display Panel -Tube

Walgreens Advanced Healing Ointment

Petrolatum 41%

Skin Protectant

NET WT 1.75 oz (50G)